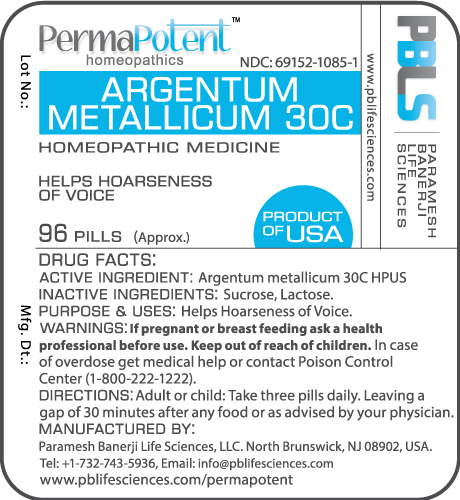 DRUG LABEL: Argentum metallicum 30C
NDC: 69152-1085 | Form: PELLET
Manufacturer: Paramesh Banerji Life Sciences LLC
Category: homeopathic | Type: HUMAN OTC DRUG LABEL
Date: 20150606

ACTIVE INGREDIENTS: SILVER 30 [hp_C]/1 1
INACTIVE INGREDIENTS: LACTOSE; SUCROSE

DRUG FACTS: Active Ingredient

Argentum metallicum 30C HPUS

Inactive Ingredients

Sucrose, Lactose

Purpose

Helps hoarseness of voice

Uses

Helps hoarseness of voice

Warnings

If pregnant or breast feeding ask a health professional before use.

Keep out of reach of children. In case of overdose get medical help or contact Poison Control Center (1-800-222-1222).

Direction

Adult or child: Take three pills daily. Leaving a gap of 30 minutes after any food or as advised by your physician.

Manufactured by

Paramesh Banerji Life Sciences, LLC.
North Brunswick, NJ 08902, USA.
Tel: +1-732-743-5936,
Email: info@pblifesciences.com
www.pblifesciences.com/permapotent

Principal Display Panel

NDC: 69152-1085-1
Argentum metallicum 30C
Homeopathic Medicine
Helps hoarseness of voice
96 Pills (Approx.)

Product of USA